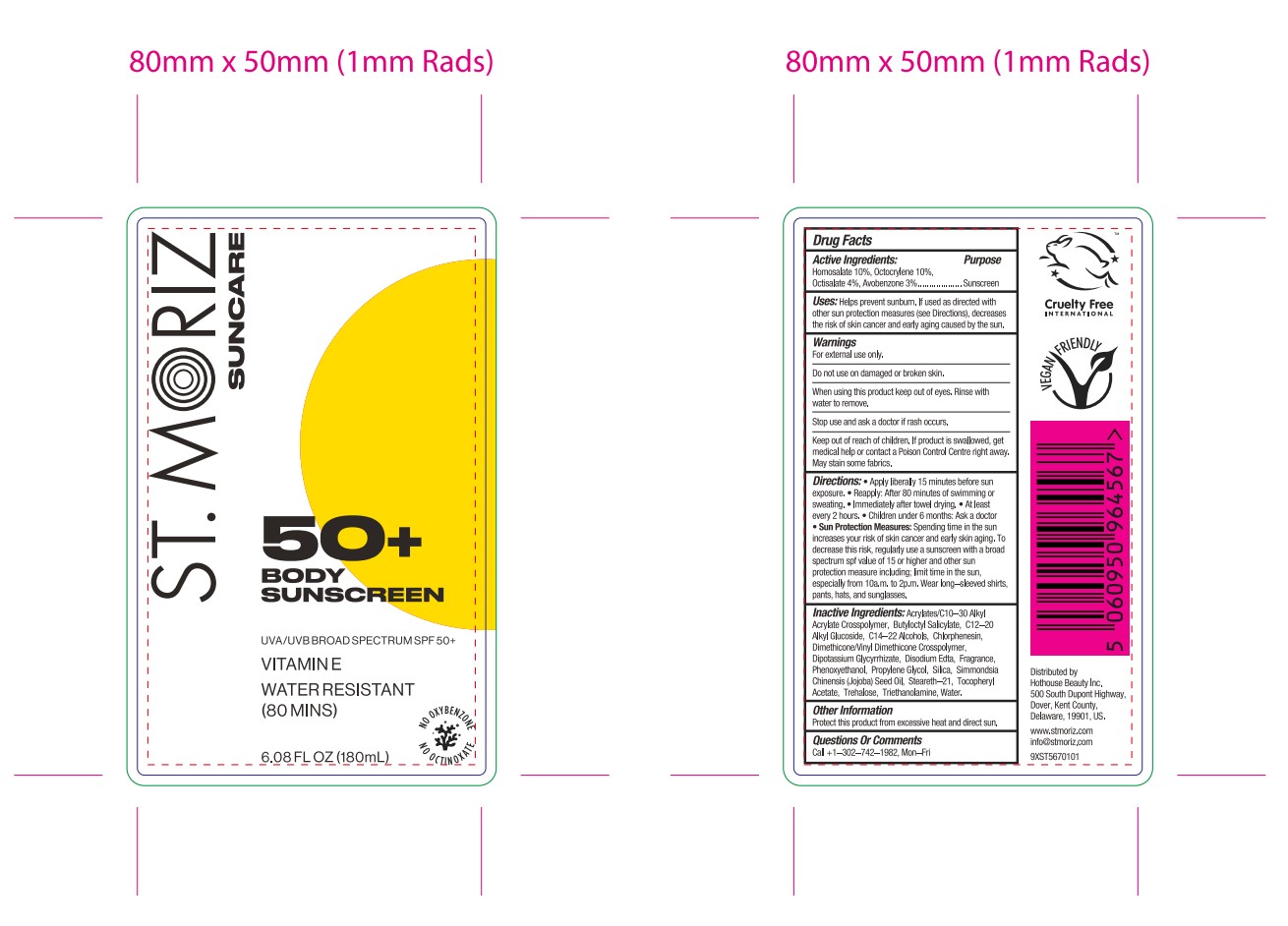 DRUG LABEL: St Moriz suncare body sunscreen spf50
NDC: 82723-014 | Form: LOTION
Manufacturer: Aopline Health Industry Technology (Guangzhou) Co., Ltd.
Category: otc | Type: HUMAN OTC DRUG LABEL
Date: 20250126

ACTIVE INGREDIENTS: HOMOSALATE 18 mg/180 mL; AVOBENZONE 5.4 mg/180 mL; OCTISALATE 7.2 mg/180 mL; OCTOCRYLENE 18 mg/180 mL
INACTIVE INGREDIENTS: WATER; CHLORPHENESIN; STEARETH-21; TRIETHANOLAMINE; PROPYLENE GLYCOL; DIMETHICONE/VINYL DIMETHICONE CROSSPOLYMER (SOFT PARTICLE); EDETATE DISODIUM; C14-22 ALCOHOLS; BUTYLOCTYL SALICYLATE; ACRYLATES/C10-30 ALKYL ACRYLATE CROSSPOLYMER (60000 MPA.S); DIPOTASSIUM GLYCYRRHIZATE; ALPHA-TOCOPHEROL ACETATE; SIMMONDSIA CHINENSIS (JOJOBA) SEED OIL; TREHALOSE; SILICA; PHENOXYETHANOL; C12-20 ALKYL GLUCOSIDE

active

HOMOSALATE
OCTOCRYLENE
OCTISALATE
AVOBENZONE

INACTIVE INGREDIENT

PROPYLENE GLYCOL
WATER
C14-22 ALCOHOLS
C12-20 ALKYL GLUCOSIDE
BUTYLOCTYL SALICYLATE
STEARETH-21
TREHALOSE
DIMETHICONE/VINYL DIMETHICONE CROSSPOLYMER
SILICA
PHENOXYETHANOL
ACRYLATES/C10-30 ALKYL ACRYLATE CROSSPOLYMER
TRIETHANOLAMINE
CHLORPHENESIN
DIPOTASSIUM GLYCYRRHIZATE
FRAGRANCE
DISODIUM EDTA
TOCOPHERYL ACETATE
SIMMONDSIA CHINENSIS (JOJOBA) SEED OIL

Purpose

Helps prevent sunbum, if used as directed withoWer sun 0rotacton measures isee Dirccans. 0ecreasethe risk of skin cancer and early aging caused by the sun,

WARNINGS

For extemal use only.Do not use on damaged or broken skin.When using this product keep out of eyes, hinse withwater to remoNe,Siop use and ask a doctor if rash cccurs,Keap out of reach of children, lf product is swallowed, getnedical help or conlact a Potson Control Cenire right away

Do not use on damaged or broken skin.

Stop use and ask a doctor if rash cccurs,

KEEP OUT OF REACH OF CHILDREN

Keap out of reach of children, lf product is swallowed, getnedical help or conlact a Potson Control Cenire right away

WHEN USING

Apply liberaly 15 minutes before su:xposure, * Reapply: After 80 minutes of swimming cely alfler towel drying. At leas!weating.e lmivery 2 hours, * Children under 6 months: Ask a dock

INDICATIONS AND USAGE

Directions: * Apply liberaly 15 minutes before sunexposure, e Reapply: After 80 minutes of swimming orsweating, " |mmedately afler towel drying," At leastevery 2 hours, * Children under 6 months: Ask a docior. Sun Protection Measures:Spending time in the sunincreases your risk of skin canoer and carly skin aging, Todecrease this risk, regulary use a sunscreen with a broadsoectrum spf value of 15 or higher and other sunprotection measure including, lmit time in the sun,especially from 10a.m, to 2p.m, Wear long-sleeved shirtspants, hats, and sunglasses,

DOSAGE AND ADMINISTRATION

Directions: * Apply liberaly 15 minutes before sunexposure, e Reapply: After 80 minutes of swimming orsweating, " |mmedately afler towel drying," At leastevery 2 hours, * Children under 6 months: Ask a docior. Sun Protection Measures: $pending time in the sunincreases your risk of skin canoer and carly skin aging, Todecrease this risk, regulary use a sunscreen with a broadsoectrum spf value of 15 or higher and other sunprotection measure including, lmit time in the sun,especially from 10a.m, to 2p.m, Wear long-sleeved shirtspants, hats, and sunglasses,